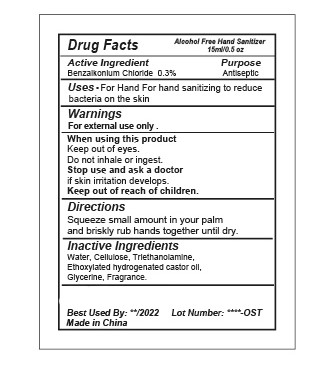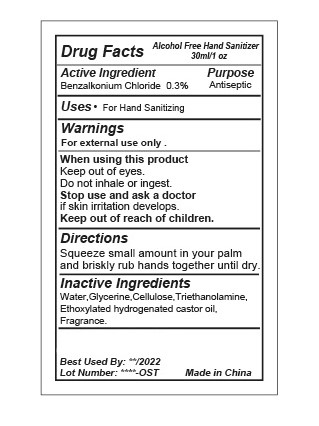 DRUG LABEL: ALCOHOL FREE HAND SANITIZER
NDC: 47993-402 | Form: GEL
Manufacturer: NINGBO JIANGBEI OCEAN STAR TRADING CO.,LTD
Category: otc | Type: HUMAN OTC DRUG LABEL
Date: 20201105

ACTIVE INGREDIENTS: BENZALKONIUM CHLORIDE 0.3 g/100 mL
INACTIVE INGREDIENTS: WATER; GLYCERIN; CARBOXYMETHYLCELLULOSE SODIUM; TRIETHANOLAMINE BENZOATE; HYDROGENATED CASTOR OIL

47993-402

Active ingredients

Benzalkonium Chloride 0.3%

PURPOSE

Antiseptic

Uses：

For hand sanitizing.

Warnings:

For external use only.

When using this product Keep out of eyes. Do not inhale or ingest.

Stop use and ask a doctor if skin irritation develops.

Keep out of reach of children.

Directions:

Squeeze small amount in your palm and briskly rub hands together until dry.

Inactive Ingredients:

Water,Glycerine,Cellulose,Triethanolamine,Ethoxylated hydrogenated castor oil,Fragrance.